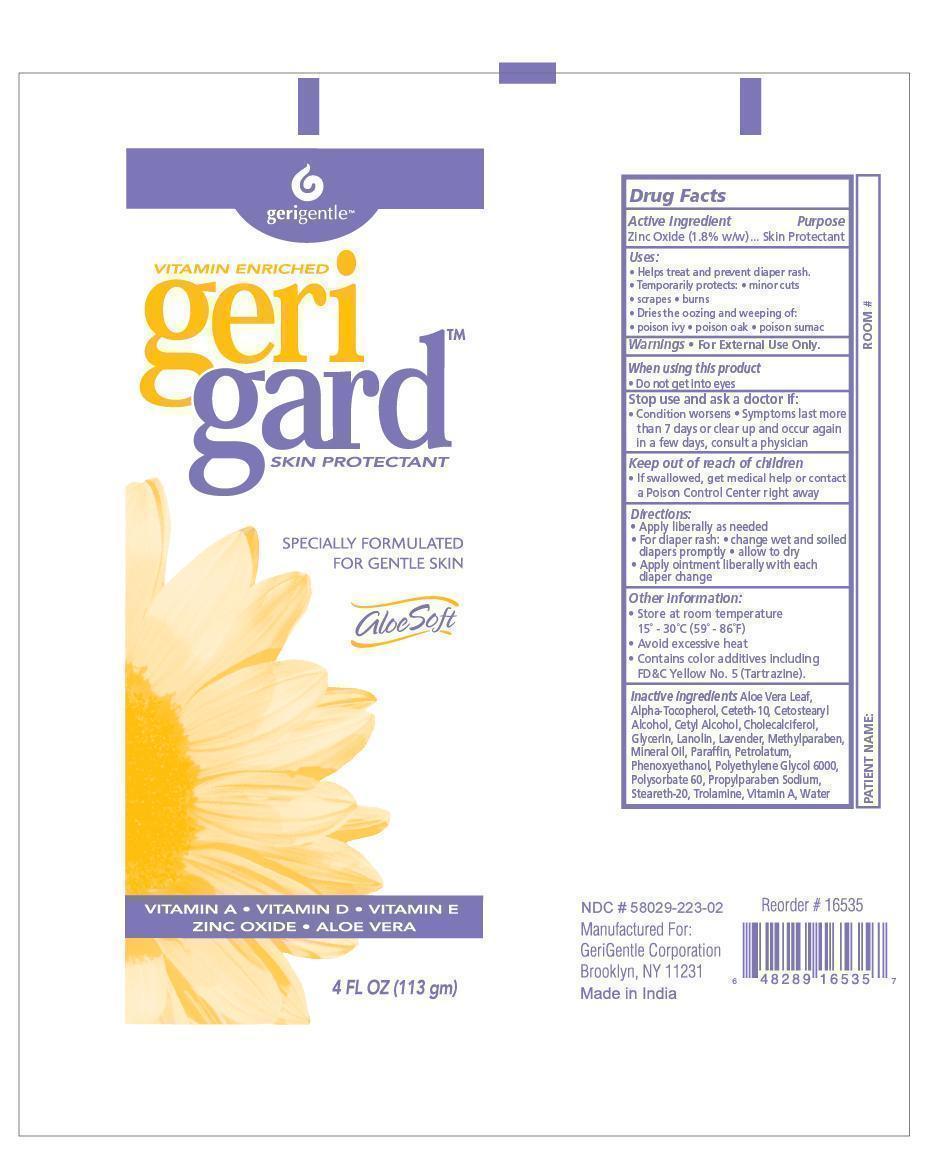 DRUG LABEL: zinc oxide
NDC: 58029-223 | Form: OINTMENT
Manufacturer: Gerimedix Incorporated
Category: otc | Type: HUMAN OTC DRUG LABEL
Date: 20140904

ACTIVE INGREDIENTS: ZINC OXIDE 1.8 g/100 g
INACTIVE INGREDIENTS: LANOLIN; CETETH-20; MINERAL OIL; PARAFFIN; METHYLPARABEN; PROPYLPARABEN SODIUM; GLYCERIN; PHENOXYETHANOL; CETYL ALCOHOL; STEARETH-20; POLYETHYLENE GLYCOL 6000; POLYSORBATE 60; CETOSTEARYL ALCOHOL; CHOLECALCIFEROL; VITAMIN A; ALPHA-TOCOPHEROL; ALOE VERA LEAF; PETROLATUM; TROLAMINE; WATER

Zinc Oxide Ointment

Active Ingredient Purpose

Zinc Oxide (1.8% w/w) Skin Protectant

Purpose:

- Helps treat and prevent diaper rash
- Temporarily protects
- minor cuts
- scrapes and
- burns
- dries the oozing and weeping of
- poison ivy
- poison oak
- poison sumac

Warnings:

For External Use Only.

When using this product:

Do not get in eyes.

Stop use and ask a doctor if:

- condition worsens
- symptoms last more than 7 days or clear up and occur again in a few days, consult a physician

Dosage & Administration

For skin protectant:
Apply liberally as needed
For diaper Rash:
change wet and soiled diapers promptly
allow to dry
apply ointment liberally with each diaper change

Keep out of reach of children.

If swallowed, get medical help or contact a Poison Control Center right away.

Other information:

- Store at room temperature
- avoid excessive heat
- contains color additives including FDC yellow # 5

Indications & Usage

Indications: For use as a general skin protectant and diaper rash.

Inactive Ingredients

Aloe Vera Leaf, Alpha-Tocopherol, Ceteth-10, Cetostearyl Alcohol, Cetyl Alcohol, Cholecalciferol, Glycerin, Lanolin, Lavender, Methylparaben, Mineral Oil, Paraffin, Petrolatum, Phenoxyethanol, Polyethylene Glycol 6000, Polysorbate 60, Propylparaben Sodium, Steareth-20, Trolamine, Vitamin A, Water

Principle Display Panel

Geriguard Skin Protectant

Zinc Oxide Ointment

zinc_oxide.jpg